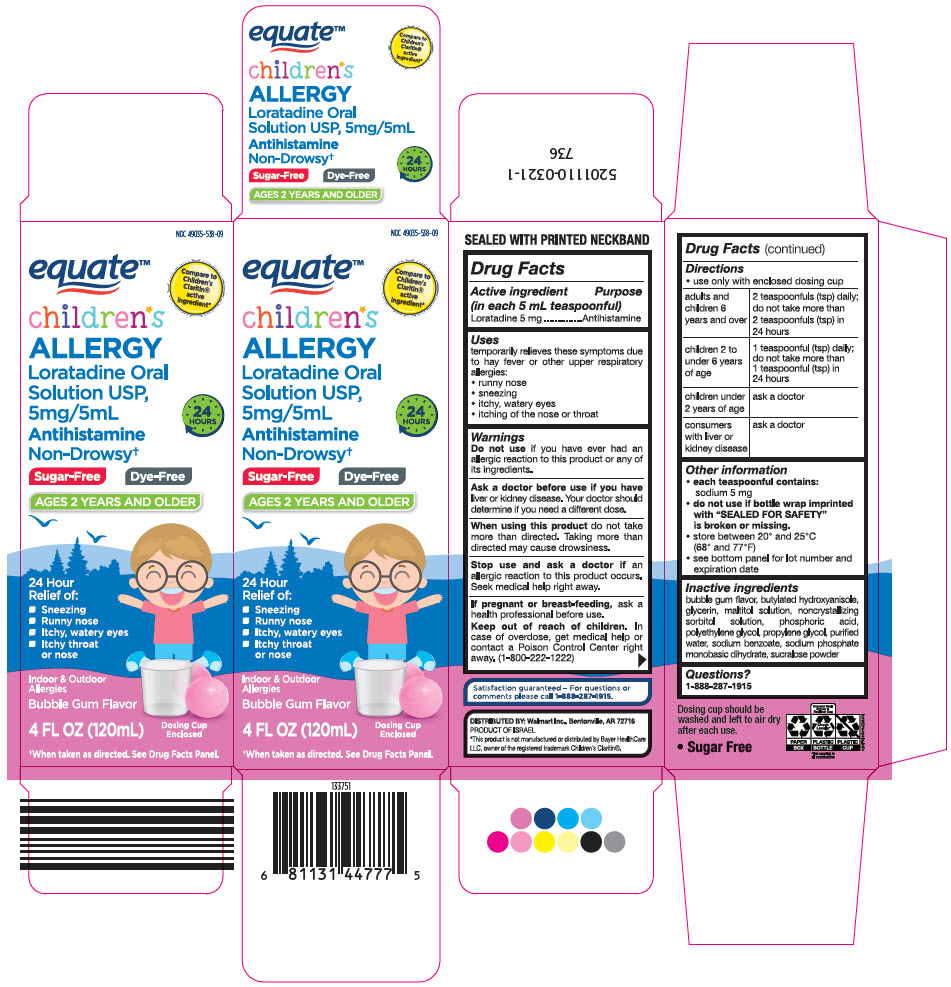 DRUG LABEL: Childrens Allergy
NDC: 49035-538 | Form: SOLUTION
Manufacturer: Wal-Mart Stores Inc
Category: otc | Type: HUMAN OTC DRUG LABEL
Date: 20210415

ACTIVE INGREDIENTS: Loratadine 5 mg/5 mL
INACTIVE INGREDIENTS: butylated hydroxyanisole; glycerin; maltitol; sorbitol; POLYETHYLENE GLYCOL, UNSPECIFIED; phosphoric acid; propylene glycol; water; sodium benzoate; SODIUM PHOSPHATE, MONOBASIC, DIHYDRATE; SUCRALOSE

Children*s Allergy

Drug Facts

Active ingredient (in each 5 mL teaspoonful)

Loratadine 5 mg

Purpose

Antihistamine

Uses

temporarily relieves these symptoms due to hay fever or other upper respiratory allergies:

- runny nose
- sneezing
- itchy, watery eyes
- itching of the nose or throat

Warnings

Do not use if you have ever had an allergic reaction to this product or any of its ingredients.

Ask a doctor before use if you have liver or kidney disease. Your doctor should determine if you need a different dose.

When using this product do not take more than directed. Taking more than directed may cause drowsiness.

Stop use and ask a doctor if an allergic reaction to this product occurs. Seek medical help right away.

PREGNANCY OR BREAST FEEDING

If pregnant or breast-feeding, ask a health professional before use.

Keep out of reach of children. In case of overdose, get medical help or contact a Poison Control Center right away. (1-800-222-1222)

Directions

- use only with enclosed dosing cup

adults and children 6 years and over | 2 teaspoonfuls (tsp) daily; do not take more than 2 teaspoonfuls (tsp) in 24 hours
children 2 to under 6 years of age | 1 teaspoonful (tsp) daily; do not take more than 1 teaspoonful (tsp) in 24 hours
children under 2 years of age | ask a doctor
consumers with liver or kidney disease | ask a doctor

Other information

- each teaspoonful contains:
  sodium 5 mg
- do not use if bottle wrap imprinted with "SEALED FOR SAFETY" is broken or missing.
- store between 20° and 25°C (68° and 77°F)
- see bottom panel for lot number and expiration date

Inactive ingredients

bubble gum flavor, butylated hydroxyanisole, glycerin, maltitol solution, noncrystallizing sorbitol solution, phosphoric acid, polyethylene glycol, propylene glycol, purified water, sodium benzoate, sodium phosphate monobasic dihydrate, sucralose powder

Questions?

1-888-287-1915

DISTRIBUTED BY: Walmart Inc., Bentonville, AR 72716

PRINCIPAL DISPLAY PANEL - 120 mL Bottle Carton

NDC 49035-538-09

equate™

Compare to
Children's
Claritin®
active
ingredient*

children*s
ALLERGY

Loratadine Oral
Solution USP,
5mg/5mL

Antihistamine

Non-Drowsy†

24
HOURS

Sugar-Free
Dye-Free

AGES 2 YEARS AND OLDER

24 Hour
Relief of:

- Sneezing
- Runny nose
- Itchy, watery eyes
- Itchy throat
  or nose

Indoor & Outdoor
Allergies

Bubble Gum Flavor

4 FL OZ (120mL)

Dosing Cup
Enclosed

†When taken as directed. See Drug Facts Panel.